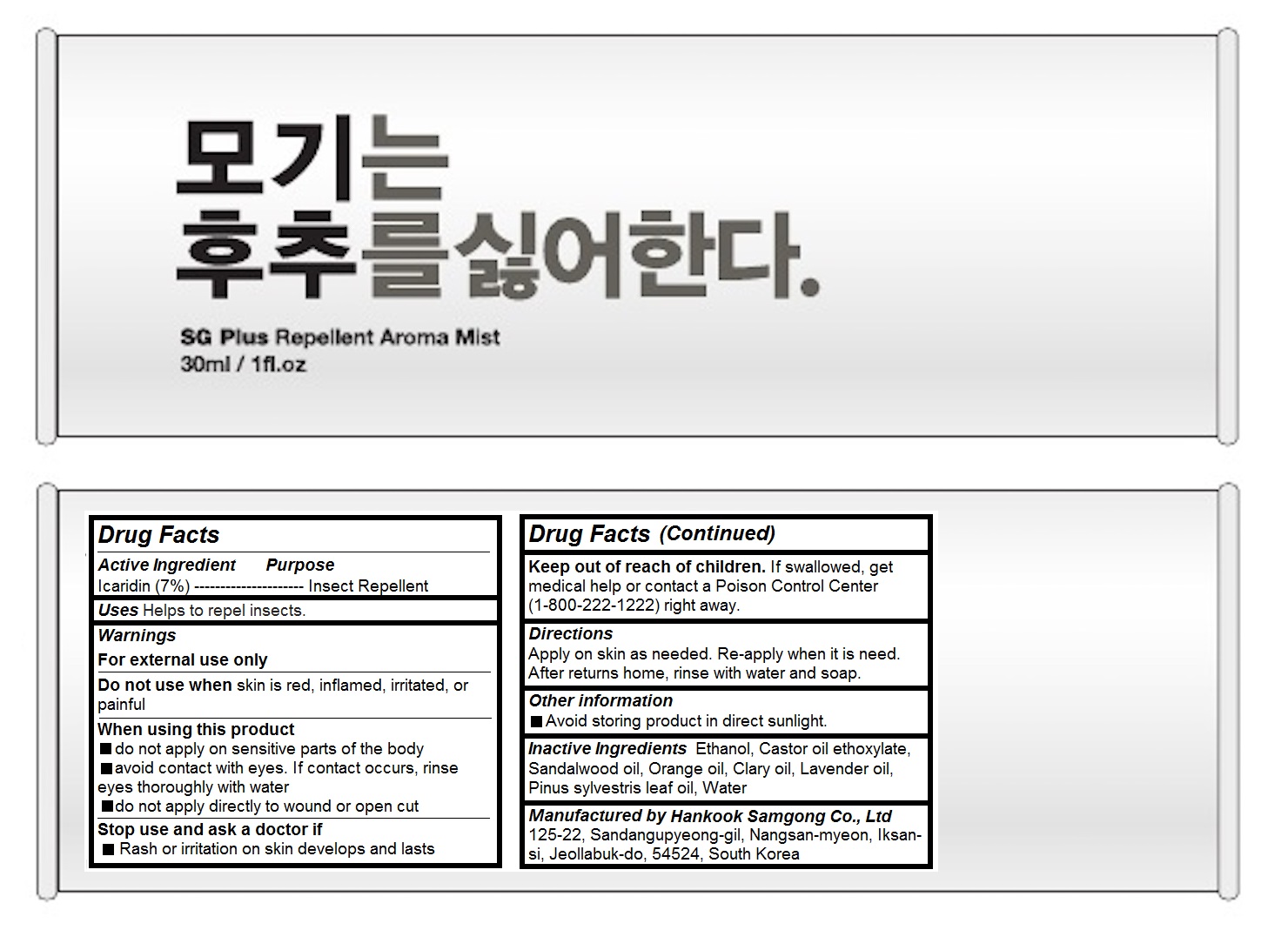 DRUG LABEL: SG Plus Repellent Aroma Mist
NDC: 71487-101 | Form: LIQUID
Manufacturer: HANKOOK SAMGONG CO.,LTD
Category: otc | Type: HUMAN OTC DRUG LABEL
Date: 20190107

ACTIVE INGREDIENTS: ICARIDIN 2.1 g/30 mL
INACTIVE INGREDIENTS: ALCOHOL; CASTOR OIL	; SANDALWOOD OIL	; CLARY SAGE OIL; LAVENDER OIL; PINE NEEDLE OIL (PINUS SYLVESTRIS); WATER

SG Plus Repellent Aroma Mist

Active Ingredients

Icaridin (7%)

Purpose

Insect Repellent

Keep out of reach of children

If swallowed, get medical help or contact a Poison Control Center (1-800-222-1222) right away.

Uses

Helps to repel insects

Directions

Apply on skin as needed. Re-apply when it is need. After returns home, rinse with water and soap.

Warnings

For external use only

Do not use when skin is red, inflamed, irritated, or painful

When using this product do not apply on sensitive parts of the body avoid contact with eyes. If contact occurs, rinse eyes thoroughly with water do not apply directly to wound or open cut Stop use and ask a doctor if Rash or irritation on skin develops and lasts

Inactive Ingredients

Ethanol, Castor oil ethoxylate, Sandalwood oil, Orange oil, Clary oil, Lavender oil, Pinus sylvestris leaf oil, Water